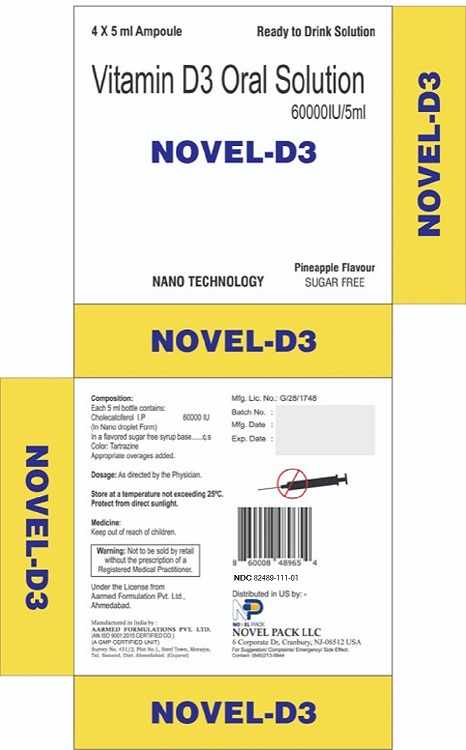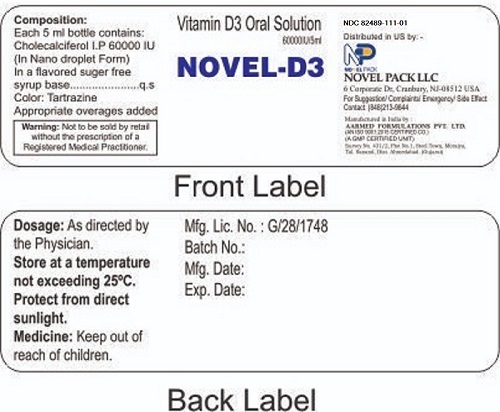 DRUG LABEL: Novel-D3
NDC: 82489-111 | Form: SOLUTION
Manufacturer: Novel Pack LLC
Category: other | Type: Dietary Supplement
Date: 20220430

ACTIVE INGREDIENTS: CHOLECALCIFEROL 60000 [iU]/1 1

Novel-D3
Vitamin D3 Oral Solution

STATEMENT OF IDENTITY

Vitamin D3 Oral Solution 60000IU/5ml

Dosage

As directed by the Physician

SAFE HANDLING WARNING

Store at a temperature not exceeding 25°C.

Protect from direct sunlight

Keep out of reach of children